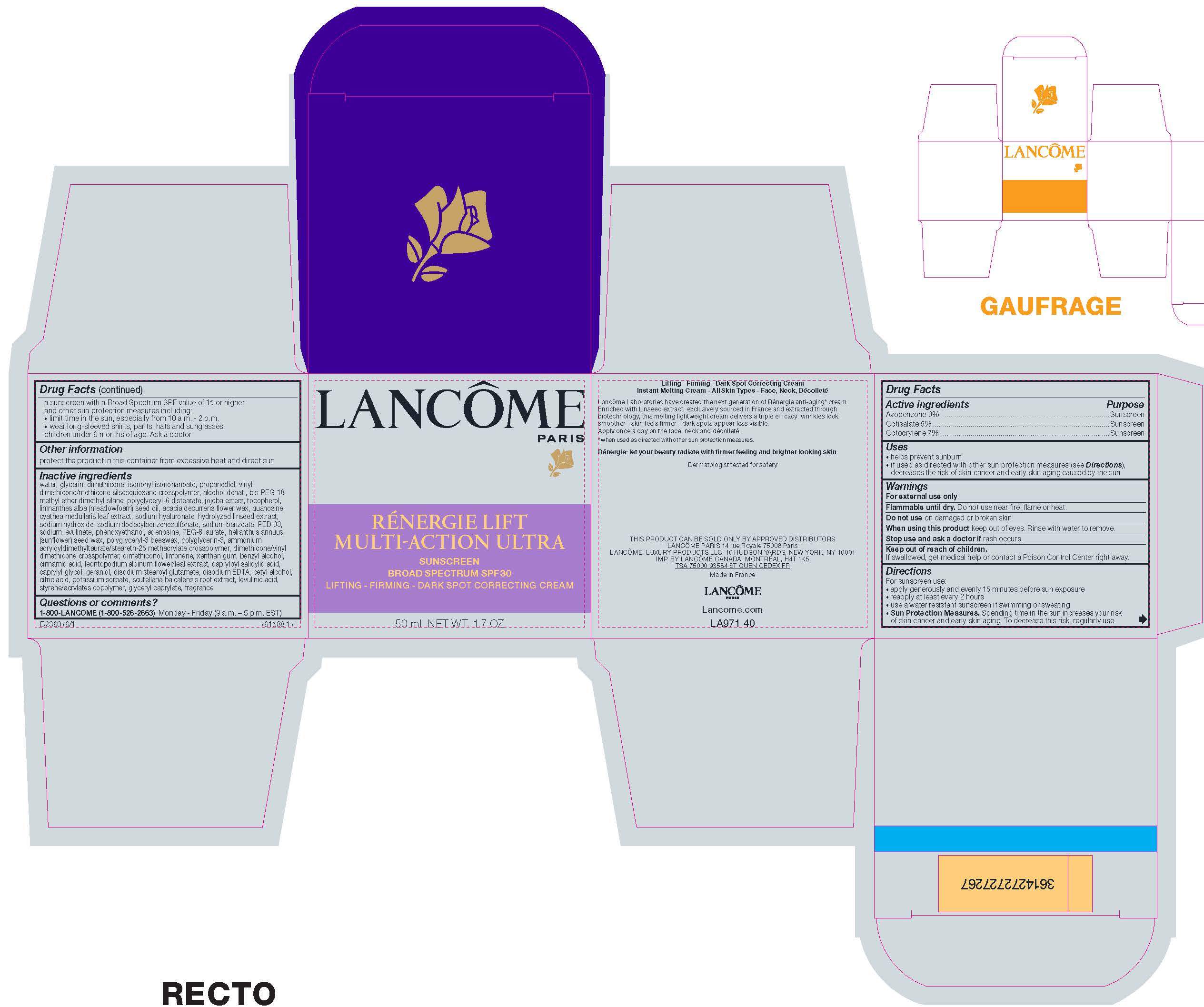 DRUG LABEL: Lancome Paris Renergie Lift MultiAction Ultra Lifting Firming Dark Spot Correcting Broad Spectrum SPF 30 Sunscreen
NDC: 49967-726 | Form: CREAM
Manufacturer: L'Oreal USA Products Inc
Category: otc | Type: HUMAN OTC DRUG LABEL
Date: 20240626

ACTIVE INGREDIENTS: Avobenzone 30 mg/1 g; Octisalate 50 mg/1 g; Octocrylene 70 mg/1 g
INACTIVE INGREDIENTS: WATER; GLYCERIN; DIMETHICONE; ISONONYL ISONONANOATE; PROPANEDIOL; VINYL DIMETHICONE/METHICONE SILSESQUIOXANE CROSSPOLYMER; ALCOHOL; BIS-PEG-18 METHYL ETHER DIMETHYL SILANE; POLYGLYCERYL-6 DISTEARATE; HYDROLYZED JOJOBA ESTERS (ACID FORM); TOCOPHEROL; MEADOWFOAM SEED OIL; ACACIA DECURRENS FLOWER WAX; GUANOSINE; CYATHEA MEDULLARIS LEAF; HYALURONATE SODIUM; SODIUM HYDROXIDE; SODIUM DODECYLBENZENESULFONATE; SODIUM BENZOATE; D&C RED NO. 33; SODIUM LEVULINATE; PHENOXYETHANOL; ADENOSINE; PEG-8 LAURATE; POLYGLYCERIN-3; DIMETHICONE/VINYL DIMETHICONE CROSSPOLYMER (HARD PARTICLE); DIMETHICONOL (100000 CST); LIMONENE, (+)-; XANTHAN GUM; BENZYL ALCOHOL; CINNAMIC ACID; LEONTOPODIUM NIVALE SUBSP. ALPINUM FLOWERING TOP; CAPRYLOYL SALICYLIC ACID; CAPRYLYL GLYCOL; GERANIOL; DISODIUM STEAROYL GLUTAMATE; EDETATE DISODIUM; CETYL ALCOHOL; CITRIC ACID MONOHYDRATE; POTASSIUM SORBATE; SCUTELLARIA BAICALENSIS ROOT; LEVULINIC ACID; STYRENE/ACRYLAMIDE COPOLYMER (500000 MW); GLYCERYL CAPRYLATE

Drug Facts

Active ingredients

Avobenzone 3%

Octisalate 5%

Octocrylene 7%

Purpose

Sunscreen

Uses

- helps prevent sunburn
- if used as directed with other sun protection measures (see Directions), decreases the risk of skin cancer and early skin aging caused by the sun

Warnings

For external use only

Flammable until dry.

Do not use near fire, flame or heat.

Do not use

on damaged or broken skin

When using this product

keep out of eyes. Rinse with water to remove.

Stop use and ask a doctor if

rash occurs

Keep out of reach of children.

If swallowed, get medical help or contact a Poison Control Center right away.

Directions

For sunscreen use:
● apply generously and evenly 15 minutes before sun exposure
● reapply at least every 2 hours
● use a water resistant sunscreen if swimming or sweating
● Sun Protection Measures. Spending time in the sun increases your risk of skin cancer and early skin aging. To decrease this risk, regularly use a sunscreen with a Broad Spectrum SPF value of 15 or higher and other sun protection measures including:
● limit time in the sun, especially from 10 a.m. – 2 p.m.
● wear long-sleeved shirts, pants, hats, and sunglasses
● children under 6 months of age: Ask a doctor

Other information

- protect the product in this container from excessive heat and direct sun

Inactive ingredients

water, glycerin, dimethicone, isononyl isononanoate, propanediol, vinyl dimethicone/methicone silsesquioxane crosspolymer, alcohol denat., bis-PEG-18 methyl ether dimethyl silane, polyglyceryl-6 distearate, jojoba esters, tocopherol, limnanthes alba (meadowfoam) seed oil, acacia decurrens flower wax, guanosine, cyathea medullaris leaf extract, sodium hyaluronate, hydrolyzed linseed extract, sodium hydroxide, sodium dodecylbenzenesulfonate, sodium benzoate, RED 33, sodium levulinae, phenoxyethanol, adenosine, PEG-8 laurate, helianthus annuus (sunflower) seed wax, polyglyceryl-3 beeswax, polyglycerin-3, ammonium acryloyldimethyltaurae/steareth-25 methacrylate crosspolymer, dimethicone/vinyl dimethicone crosspolyer, dimethiconol, limonene, xanthan gum, benzyl alcohol, cinnamic acid, leontopodium alpinum flower/leaf extract, capryloyl salicylic acid, caprylyl glycol, geraniol, disodium stearoyl glutamate, disodium EDTA, cetyl alcohol, citric acid, potassium sorbate, sculellaria baicalensis root extract, levulinic acid, styrene/acrylaes copolymer, clyberyl caprylate, fragrance

Questions or comments?

1-800-LANCOME (1-800-526-2663) Monday - Friday (9 a.m. - 5 p.m. EST)